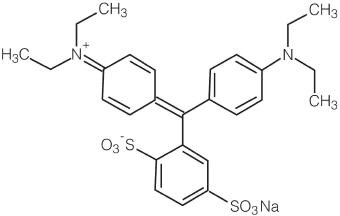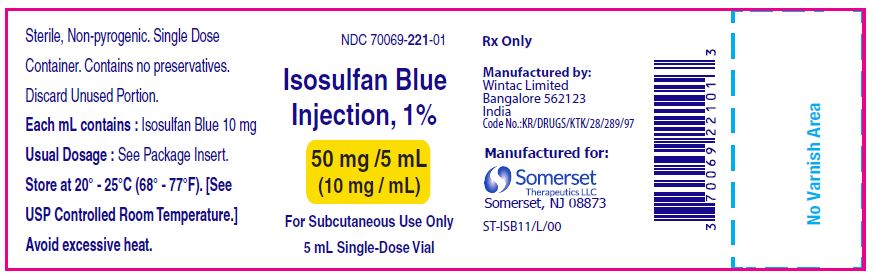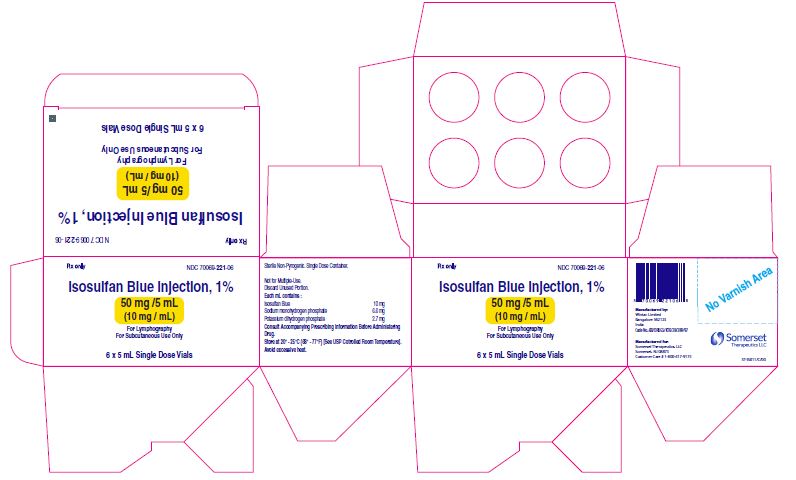 DRUG LABEL: Isosulfan Blue
NDC: 70069-221 | Form: INJECTION, SOLUTION
Manufacturer: Somerset Therapeutics, LLC
Category: prescription | Type: HUMAN PRESCRIPTION DRUG LABEL
Date: 20250109

ACTIVE INGREDIENTS: ISOSULFAN BLUE 10 mg/1 mL
INACTIVE INGREDIENTS: POTASSIUM PHOSPHATE, MONOBASIC 2.7 mg/1 mL; SODIUM PHOSPHATE, DIBASIC, ANHYDROUS 6.6 mg/1 mL; WATER

HIGHLIGHTS OF PRESCRIBING INFORMATION

These highlights do not include all the information needed to use ISOSULFAN BLUE INJECTION, 1% safely and effectively. See full prescribing information for ISOSULFAN BLUE INJECTION 1%.
ISOSULFAN BLUE Injection, for subcutaneous use
Initial U.S. Approval: 1981

RECENT MAJOR CHANGES

Warnings and Precautions, Interference with Oxygen Saturation and Methemoglobin Measurements (5.3). 10/2007

1 INDICATIONS AND USAGE

Isosulfan blue injection 1% upon subcutaneous administration, delineates the lymphatic vessels draining the region of injection. It is an adjunct to lymphography in: primary and secondary lymphedema of the extremities; chyluria, chylous ascites or chylothorax; lymph node involvement by primary or secondary neoplasm; lymph node response to therapeutic modalities (1.1).

2 DOSAGE AND ADMINISTRATION

Isosulfan blue injection 1% is to be administered subcutaneously, one-half (1/2) mL into three (3) interdigital spaces of each extremity per study. A maximum dose of 3 mL (30 mg) isosulfan blue is, therefore, injected (2.1).

3 DOSAGE FORMS AND STRENGTHS

1% aqueous solution (isosulfan blue)

4 CONTRAINDICATIONS

Hypersensitivity to triphenylmethane or related compounds.

5 WARNINGS AND PRECAUTIONS

- Life threatening anaphylactic reactions have occurred after isosulfan blue injection 1% administration. Monitor patients closely for at least 60 minutes after administration of isosulfan blue injection 1% (5.1).
- The admixture of isosulfan blue injection 1% with local anesthetics results in an immediate precipitation of 4% to 9% drug complex. Use a separate syringe for anesthetics (5.2).
- Isosulfan blue injection 1% interferes with measurements in peripheral blood pulse oximetry. Arterial blood gas analysis may be needed (5.3).

6 ADVERSE REACTIONS

Hypersensitivity Reactions: Hypersensitivity reactions occur in approximately 2% of patients and include life threatening anaphylactic reactions with respiratory distress, shock, angioedema, urticaria, pruritus. A death has been reported following IV administration of a similar compound.

To report SUSPECTED ADVERSE REACTIONS, contact Somerset Therapeutics, LLC at 1- 800-417-9175 or FDA at 1-800-FDA-1088 or www.fda.gov/medwatch

7 DRUG INTERACTIONS

No drug interactions have been identified for isosulfan blue injection 1%.

8 USE IN SPECIFIC POPULATIONS

- Caution should be exercised when isosulfan blue injection 1% is administered to nursing mothers (8.3).
- Safety and effectiveness of isosulfan blue injection 1% in children has not been established (8.4).

FULL PRESCRIBING INFORMATION

1 INDICATIONS AND USAGE

1.1 Lymphatic Vessel Delineation

Isosulfan blue injection 1% upon subcutaneous administration, delineates lymphatic vessels draining the region of injection. It is an adjunct to lymphography in: primary and secondary lymphedema of the extremities; chyluria, chylous ascites or chylothorax; lymph node involvement by primary or secondary neoplasm; and lymph node response to therapeutic modalities.

2 DOSAGE AND ADMINISTRATION

2.1 Subcutaneous administration

Isosulfan blue injection 1% is to be administered subcutaneously, one-half (1/2) mL into three (3) interdigital spaces of each extremity per study. A maximum dose of 3 mL (30 mg) isosulfan blue is, therefore, injected.

3 DOSAGE FORMS AND STRENGTHS

1% aqueous solution (isosulfan blue)

4 CONTRAINDICATIONS

Isosulfan blue injection 1% is contraindicated in those individuals with known hypersensitivity to triphenylmethane or related compounds.

5 WARNINGS AND PRECAUTIONS

5.1 Hypersensitivity Reactions

Life threatening anaphylactic reactions (respiratory distress, shock, angioedema) have occurred after isosulfan blue injection 1% administration. Reactions are more likely to occur in patients with a history of bronchial asthma, allergies, drug reactions or previous reactions to triphenylmethane dyes. Monitor patients closely for at least 60 minutes after administration of isosulfan blue injection 1%. Trained personnel should be available to administer emergency care including resuscitation.

5.2 Precipitation of Isosulfan Blue Injection 1% by Lidocaine

The admixture of isosulfan blue injection 1% (with local anesthetics (i.e. lidocaine)) in the same syringe results in an immediate precipitation of 4% to 9% drug complex. Use a separate syringe to administer a local anesthetic.

5.3 Interference with Oxygen Saturation and Methemoglobin Measurements

Isosulfan blue injection 1% interferes with measurements of oxygen saturation in peripheral blood by pulse oximetry and can cause falsely low readings. The interference effect is maximal at 30 minutes and minimal generally by 4 hours after administration. Arterial blood gas analysis may be needed to verify decreased arterial partial pressure of oxygen.

Isosulfan blue injection 1% may also cause falsely elevated readings of methemoglobin by arterial blood gas analyzer. Therefore, co-oximetry may be needed to verify methemoglobin level.

6 ADVERSE REACTIONS

6.1 Post-Marketing Experience

Hypersensitivity Reactions: Case series report an overall incidence of hypersensitivity reactions in approximately 2% of patients. Life threatening anaphylactic reactions have occurred. Manifestations include respiratory distress, shock, angioedema, urticaria, pruritus. A death has been reported following administration of a similar compound employed to estimate the depth of a severe burn. Reactions are more likely to occur in patients with a personal or family history of bronchial asthma, significant allergies, drug reactions or previous reactions to triphenylmethane dyes [see Warnings and Precautions (5)].

Laboratory Tests: Isosulfan blue injection 1% interferes with measurements of oxygen saturation by pulse oximetry and of methemoglobin by gas analyzer [see Warnings and Precautions (5)].

Skin: transient or long-term (tattooing) blue coloration.

7 DRUG INTERACTIONS

No drug interactions have been identified with isosulfan blue injection 1%.

8 USE IN SPECIFIC POPULATIONS

8.3 Nursing Mothers

It is not known whether this drug is excreted in human milk.

Because many drugs are excreted in human milk, caution should be exercised when isosulfan blue injection 1% is administered to a nursing mother.

8.4 Pediatric Use

Safety and effectiveness of isosulfan blue injection 1% in children have not been established.

10 OVERDOSAGE

Do not exceed indicated recommended dosage as overdosage levels have not been identified for isosulfan blue injection 1%.

11 DESCRIPTION

The chemical name of isosulfan blue injection 1% is N-[4- [[4-(diethylamino)phenyl] (2,5-disulfophenyl) methylene]-2,5-cyclohexadien-1-ylidene]-N-ethylethanaminium hydroxide, inner salt, sodium salt. Its structural formula is:

Isosulfan blue injection 1% is a sterile aqueous solution for subcutaneous administration. Phosphate buffer in sterile, pyrogen free water is added in sufficient quantity to yield a final pH of 6.8 to 7.4. Each mL of solution contains 10 mg isosulfan blue, 6.6 mg sodium monohydrogen phosphate and 2.7 mg potassium dihydrogen phosphate. The solution contains no preservative. Isosulfan blue injection 1% is a contrast agent for the delineation of lymphatic vessels.

12 CLINICAL PHARMACOLOGY

12.2 Pharmacodynamics

Following subcutaneous administration, isosulfan blue injection 1% binds to serum proteins and is picked up by the lymphatic vessels. Thus, the lymphatic vessels are delineated by the blue dye.

12.3 Pharmacokinetics

Up to 10% of the subcutaneously administered dose of isosulfan blue injection 1% is excreted unchanged in the urine in 24 hours in humans.

13 NONCLINICAL TOXICOLOGY

13.1 Carcinogenesis, Mutagenesis, Impairment of Fertility

Long-term studies in animals have not been performed to evaluate the carcinogenic potential of isosulfan blue injection 1%. Reproduction studies in animals have not been conducted and, therefore, it is unknown if a problem concerning mutagenesis or impairment of fertility in either males or females exists.

13.3 Teratogenic Effects

Pregnancy Category C. Animal reproduction studies have not been conducted with isosulfan blue injection 1%. It is not known whether isosulfan blue injection 1% can cause fetal harm when administered to a pregnant woman or can affect reproduction capacity. Isosulfan blue injection 1% should be given to a pregnant woman only if clearly needed.

16 HOW SUPPLIED/STORAGE AND HANDLING

Isosulfan blue injection 1% is supplied as a 5 mL single-dose vial, 1% aqueous solution in a phosphate buffer prepared by appropriate manufacturing to be sterile and pyrogen-free.

NDC 70069-221-06

carton containing 6 x 5 mL single-dose vials

STORAGE: Store at 20° to 25°C (68° to 77°F). [See USP Controlled Room Temperature]. Avoid excessive heat.

17 PATIENT COUNSELING INFORMATION

Inform patients that urine color may be blue for 24 hours following administration of isosulfan blue injection 1%.

Manufactured By:

Wintac Limited

Bangalore 562123

India

Code No.: KR/DRUGS/KTK/28/289/97

Manufactured for:

Somerset Therapeutics, LLC

Somerset, NJ 08873

ST-ISB11/P/00

PACKAGE LABEL.PRINCIPAL DISPLAY PANEL

Container label

Carton label